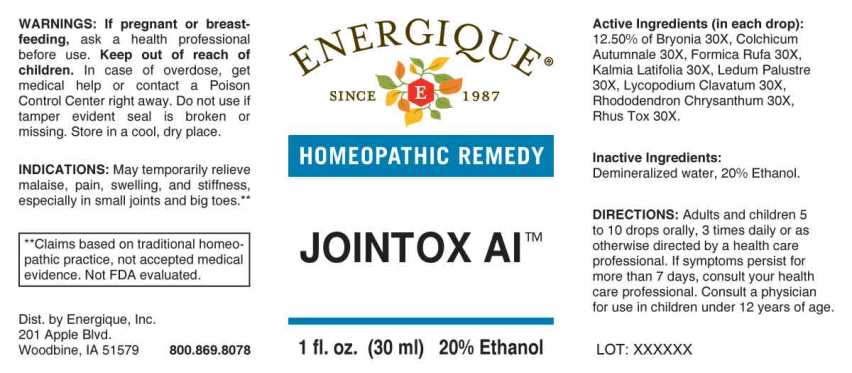 DRUG LABEL: Jointox AI
NDC: 44911-0586 | Form: LIQUID
Manufacturer: Energique, Inc.
Category: homeopathic | Type: HUMAN OTC DRUG LABEL
Date: 20240326

ACTIVE INGREDIENTS: BRYONIA ALBA ROOT 30 [hp_X]/1 mL; COLCHICUM AUTUMNALE BULB 30 [hp_X]/1 mL; FORMICA RUFA 30 [hp_X]/1 mL; KALMIA LATIFOLIA LEAF 30 [hp_X]/1 mL; LEDUM PALUSTRE TWIG 30 [hp_X]/1 mL; LYCOPODIUM CLAVATUM SPORE 30 [hp_X]/1 mL; RHODODENDRON AUREUM LEAF 30 [hp_X]/1 mL; TOXICODENDRON PUBESCENS LEAF 30 [hp_X]/1 mL
INACTIVE INGREDIENTS: WATER; ALCOHOL

DRUG FACTS:

ACTIVE INGREDIENT:

(in each drop): 12.50% of Bryonia (Alba) 30X, Colchicum Autumnale 30X, Formica Rufa 30X, Kalmia Latifolia 30X, Ledum Palustre 30X, Lycopodium Clavatum 30X, Rhododendron Chrysanthum 30X, Rhus Tox 30X.

INDICATIONS:

May temporarily relieve symptoms due to joint aches and pains, swelling, and gout.**

**Claims based on traditional homeopathic practice, not accepted medical evidence. Not FDA evaluated.

WARNINGS:

If pregnant or breast-feeding, ask a health professional before use.

Keep out of reach of children. In case of overdose, get medical help or contact a Poison Control Center right away.

Do not use if tamper evident seal is broken or missing. Store in a cool, dry place.

KEEP OUT OF REACH OF CHILDREN:

In case of overdose, get medical help or contact a Poison Control Center right away.

DIRECTIONS:

Adults and children 5 to 10 drops orally, 3 times daily or as otherwise directed by a health care professional. If symptoms persist, consult your health care professional. Consult a physician for use in children under 12 years of age.

INDICATIONS:

May temporarily relieve symptoms due to joint aches and pains, swelling, and gout.**

**Claims based on traditional homeopathic practice, not accepted medical evidence. Not FDA evaluated.

INACTIVE INGREDIENTS:

Demineralized water, 20% Ethanol

QUESTIONS:

Dist. by Energique, Inc.

201 Apple Blvd

Woodbine, IA 51579 800.869.8078

PACKAGE LABEL DISPLAY:

ENERGIQUE

SINCE 1987

HOMEOPATHIC REMEDY

JOINTOX AI

1 fl. oz. (30 ml)